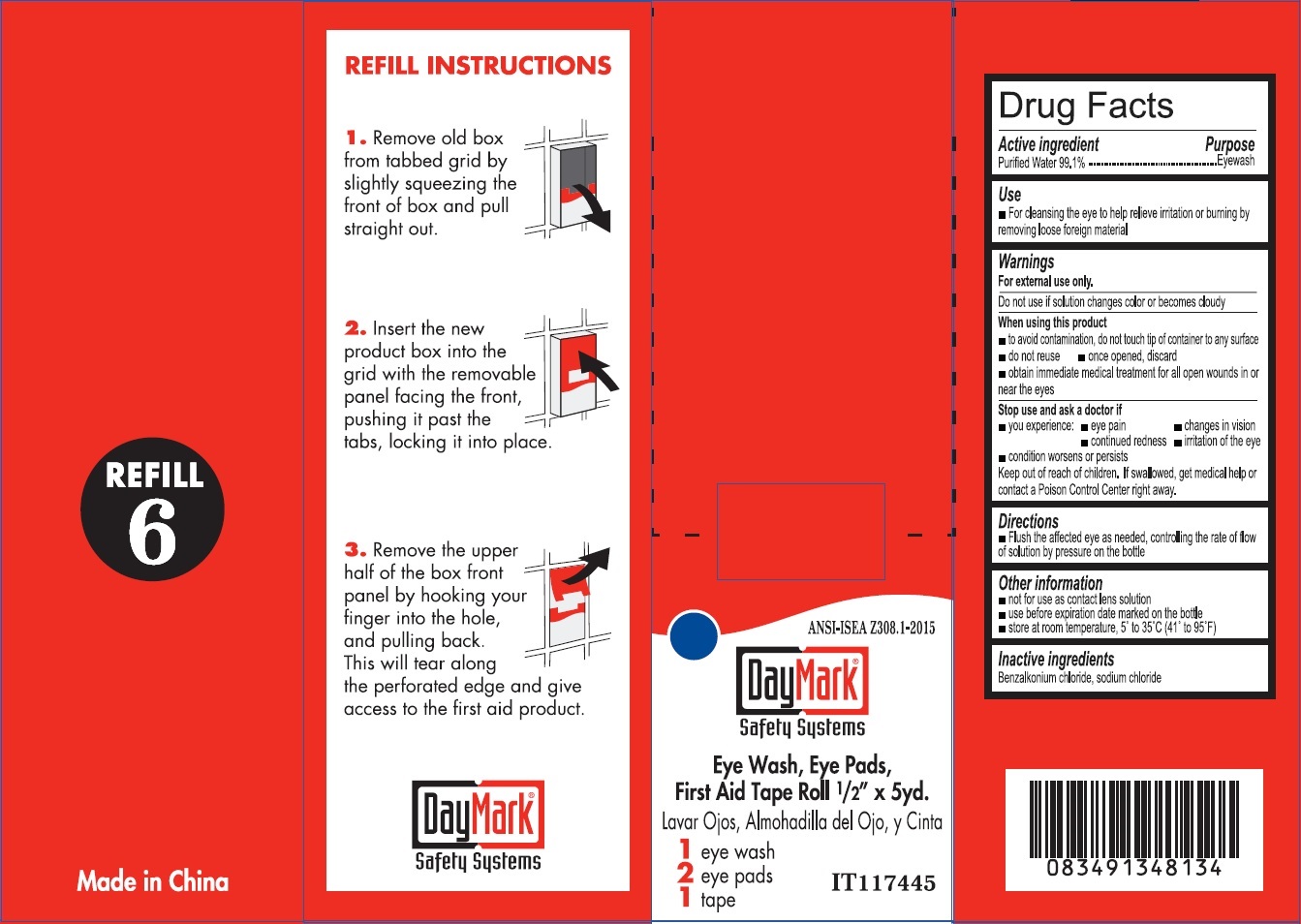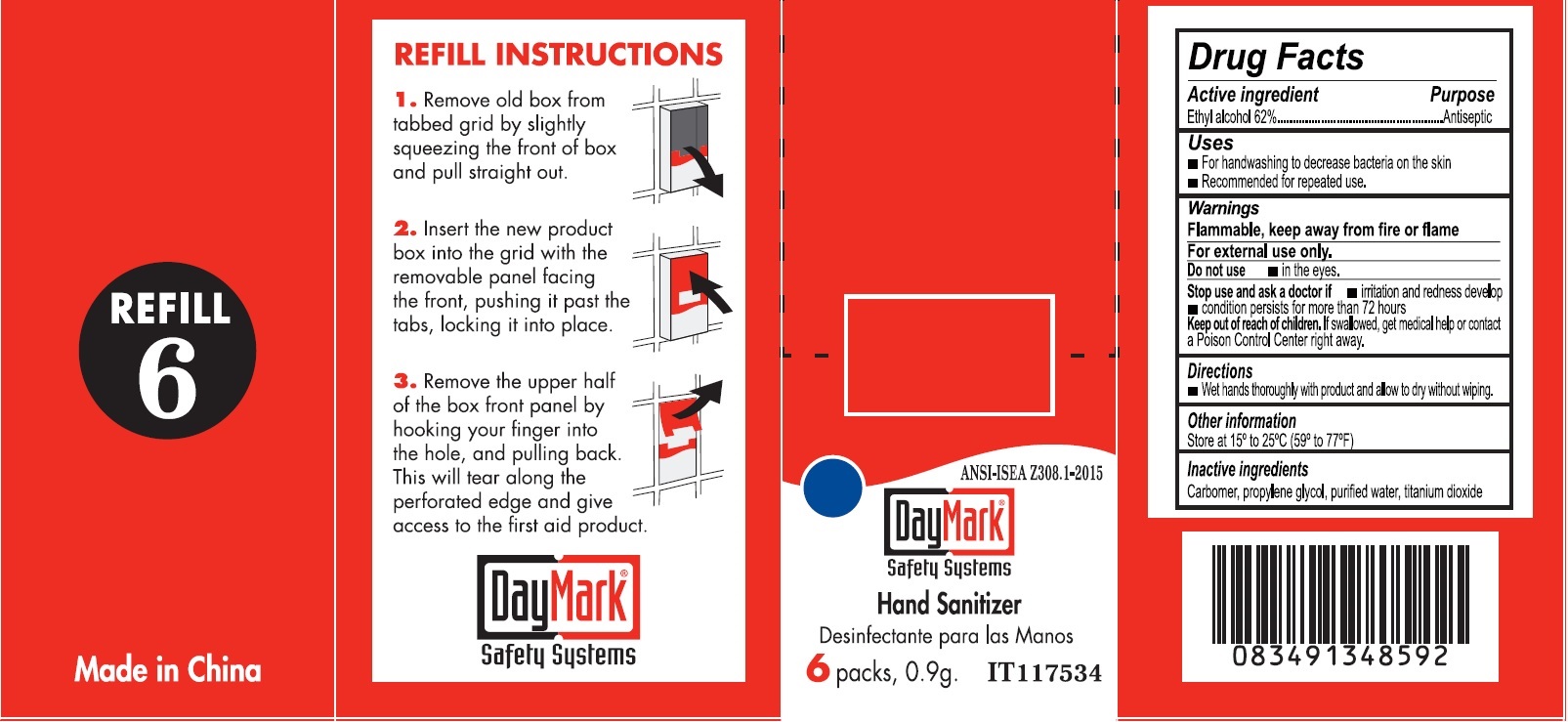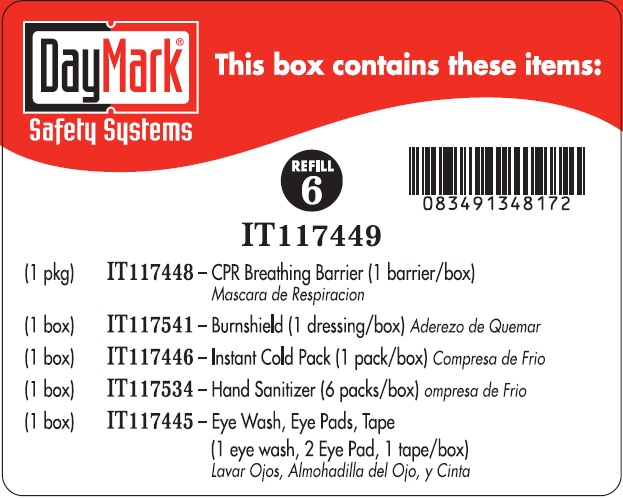 DRUG LABEL: Refill 6
NDC: 49687-0019 | Form: KIT | Route: TOPICAL
Manufacturer: CMC Group, Inc.
Category: otc | Type: HUMAN OTC DRUG LABEL
Date: 20250113

ACTIVE INGREDIENTS: ALCOHOL 0.62 g/1 g; WATER 991 mg/1 mL
INACTIVE INGREDIENTS: CARBOXYPOLYMETHYLENE; PROPYLENE GLYCOL; WATER; TITANIUM DIOXIDE; BENZALKONIUM CHLORIDE; SODIUM CHLORIDE

Refill 6

Active ingredient

Ethyl alcohol 62%

Purpose

Antiseptic

Uses

- For handwashing to decrease bacteria on the skin

- Recommended for repeated use.

Warnings

Flammable, keep away from fire or flame For external use only.

Do not use

- in the eyes.

Stop use and ask a doctor if

- irritation and redness develop

- condition persists for more than 72 hours

Keep out of reach children.

If swallowed, get medical help or contact a Poison Control Center right away.

Directions

- Wet hands thoroughly with product and allow to dry without wiping.

Other information

Store at 15° to 25°C (59° to 77°F)

Inactive ingredients

Carbomer, propylene glycol, purified water, titanium dioxide

Active ingredient

Purified Water 99.1%

Purpose

Eyewash

Use

For cleansing the eye to help relieve irritation or burning by removing loose foreign material

Warnings

For external use only.

Do not use

if solution changes color or becomes cloudy

When using this product

• to avoid contamination, do not touch tip of container to any surface • do not reuse • once opened, discard • obtain immediate medical treatment for all open wounds in or near the eyes

Stop use and ask a doctor if

• you experience: • eye pain • changes in vision • continued redness • irritation of the eye • condition worsens or persists

Keep out of reach of children.

If swallowed, get medical help or contact a Poison Control Center right away.

Directions

• Flush the affected eye as needed, controlling the rate of flow of solution by pressure on the bottle

Other information

• not for use as contact lens solution

• use before expiration date marked on the bottle

• store at room temperature, 5° to 35°C (41° to 95°F)

Inactive ingredients

Benzalkonium chloride, sodium chloride